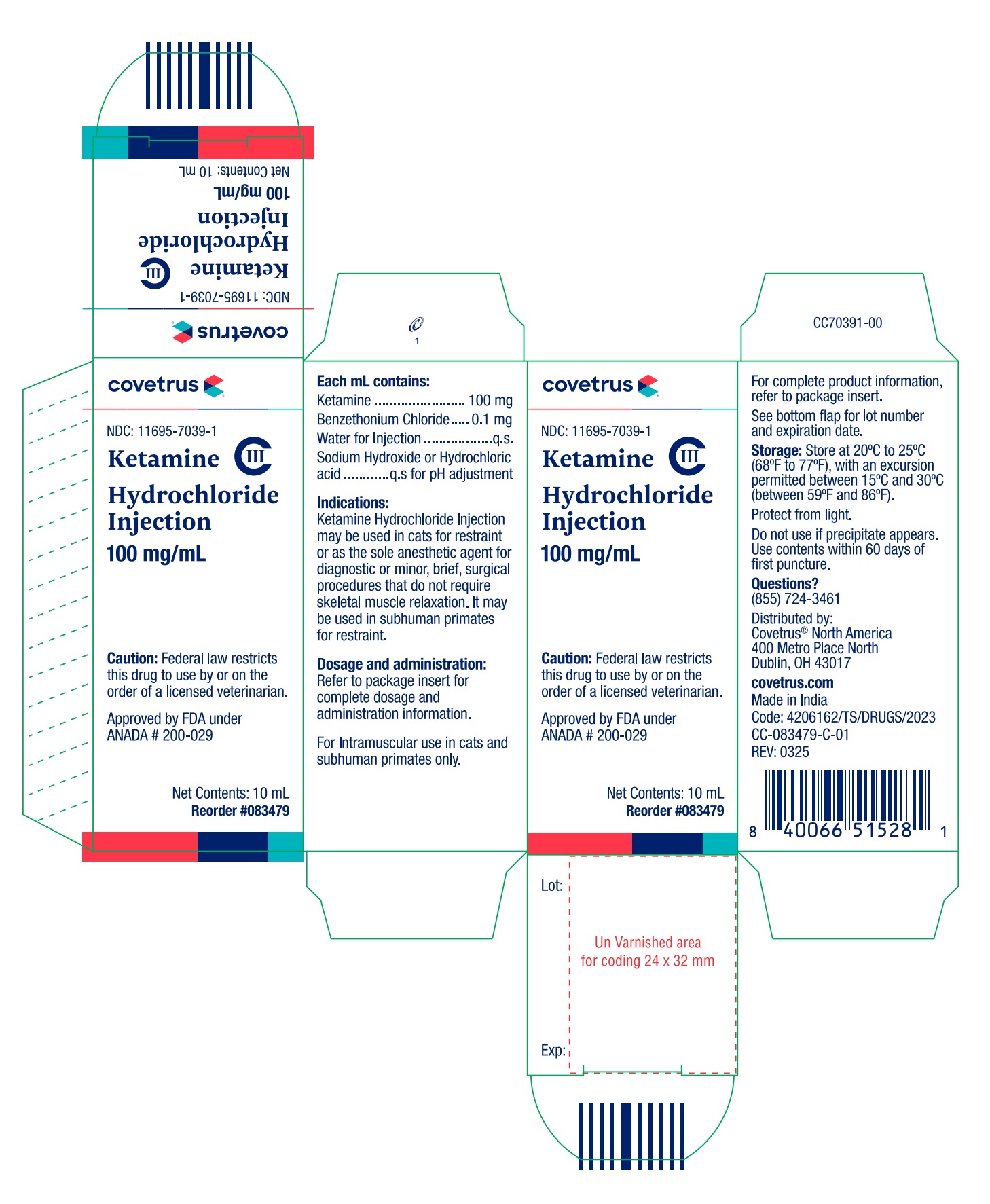 DRUG LABEL: Ketamine Hydrochloride
NDC: 11695-7039 | Form: INJECTION
Manufacturer: Covetrus
Category: animal | Type: PRESCRIPTION ANIMAL DRUG LABEL
Date: 20250909

ACTIVE INGREDIENTS: KETAMINE HYDROCHLORIDE 100 mg/1 mL

Covetrus
Ketamine Hydrochloride Injection CIII
100 mg/mL

Veterinary Injection For Intramuscular Use in Cats and Subhuman Primates Only

CAUTION

Federal law restricts this drug to use by or on the order of a licensed veterinarian.

DESCRIPTION

Ketamine Hydrochloride Injection is a rapid-acting, nonnarcotic, nonbarbiturate agent for anesthetic use in cats and for restraint in subhuman primates. It is chemically designated dl 2-(o-chlorophenyl)-2-(methylamino) cyclohexanone hydrochloride and is supplied as a slightly acid (pH 3.5 to 5.5) solution for intramuscular injection. Each mL contains 100 mg ketamine base (equivalent to 115 mg ketamine hydrochloride) and not more than 0.1 mg benzethonium chloride as a preservative. Sodium Hydroxide or Hydrochloric acid for pH adjustment and Water for injection, q.s.

INDICATIONS

Ketamine Hydrochloride Injection may be used in cats for restraint or as the sole anesthetic agent for diagnostic or minor, brief, surgical procedures that do not require skeletal muscle relaxation. It may be used in subhuman primates for restraint.

DOSAGE AND ADMINISTRATION

Ketamine Hydrochloride Injection is well tolerated by cats and subhuman primates when administered by intramuscular injection.

Fasting prior to induction of anesthesia or restraint with Ketamine Hydrochloride Injection is not essential; however, when preparing for elective surgery, it is advisable to withhold food for at least six hours prior to administration of Ketamine Hydrochloride Injection.

Anesthesia may be of shorter duration in immature cats. Restraint in subhuman primate neonates (less than 24 hours of age) is difficult to achieve.

As with other anesthetic agents, the individual response to Ketamine Hydrochloride Injection is somewhat varied depending upon the dose, general condition and age of the subject so that dosage recommendations cannot be absolutely fixed.

Dosage

Cats: A dose of 11 mg/kg (5 mg/lb) is recommended to produce restraint.
Dosages from 22 to 33 mg/kg (10 to 15 mg/lb) produce anesthesia that is suitable for diagnostic or minor surgical procedures that do not require skeletal muscle relaxation.

Subhuman Primates: The recommended restraint dosages of Ketamine Hydrochloride Injection for the following species are: Cercocebus torquatus (white-collared mangabey), Papio cynocephalus (yellow baboon), Pan troglodytes verus (chimpanzee), Papio anubis (olive baboon), Pongo pygmaeus (orangutan), Macaca nemestrina (pig-tailed macaque) 5 to 7.5 mg/kg; Presbytis entellus (entellus langur) 3 to 5 mg/kg; Gorilla gorilla gorilla (gorilla) 7 to 10 mg/kg; Aotus trivirgatus (night monkey) 10 to 12 mg/kg; Macaca mulatta (rhesus monkey) 5 to 10 mg/kg; Cebus capucinus (white-throated capuchin) 13 to 15 mg/kg; and Macaca fascicularis (crab-eating macaque), Macaca radiata (bonnet macaque) and Saimiri sciureus (squirrel monkey) 12 to 15 mg/kg.

A single intramuscular injection produces restraint suitable for TB testing; radiography, physical examination or blood collection.

CONTRAINDICATIONS

Ketamine Hydrochloride Injection is contraindicated in cats and subhuman primates suffering from renal or hepatic insufficiency.

Ketamine Hydrochloride Injection is detoxified by the liver and excreted by the kidneys; therefore, any preexistent hepatic or renal pathology or impairment of function can be expected to result in prolonged anesthesia; related fatalities have been reported.

PRECAUTIONS

In cats, doses in excess of 50 mg/kg during any single procedure should not be used. The maximum recommended dose in subhuman primates is 40 mg/kg.

To reduce the incidence of emergence reactions, animals should not be stimulated by sound or handling during the recovery period. However, this does not preclude the monitoring of vital signs.

Apnea, respiratory arrest, cardiac arrest and death have occasionally been reported with ketamine used alone, and more frequently when used in conjunction with sedatives or other anesthetics. Close monitoring of patients is strongly advised during induction, maintenance and recovery from anesthesia.

Color of solution may vary from colorless to very slightly yellowish and may darken upon prolonged exposure to light. This darkening does not affect potency. Do not use if precipitate appears.

ADVERSE REACTIONS

Respiratory depression may occur following administration of high doses of Ketamine Hydrochloride Injection. If at any time respiration becomes excessively depressed and the animal becomes cyanotic, resuscitative measures should be instituted promptly. Adequate pulmonary ventilation using either oxygen or room air is recommended as a resuscitative measure.

Adverse reactions reported have included emesis, salivation, vocalization, erratic recovery and prolonged recovery, spastic jerking movements, convulsions, muscular tremors, hypertonicity, opisthotonos, dyspnea and cardiac arrest.

In the cat, myoclonic jerking and/or mild tonic convulsions can be controlled by ultrashort-acting barbiturates which should be given to effect. The barbiturates should be administered intravenously at a dose level of one-sixth to one-fourth the usual dose for the product being used.

Acepromazine may also be used. However, recent information indicates that some phenothiazine derivatives may potentiate the toxic effects of organic phosphate compounds such as found in flea collars and certain anthelmintics. A study has indicated that ketamine hydrochloride alone does not potentiate the toxic effects of organic phosphate compounds.

To report suspected adverse drug experiences, for technical assistance or to obtain a copy of the Safety Data Sheet, contact Covetrus® North America at (855) 724-3461 or covetrus.com.

For additional information about adverse drug experience reporting for animal drugs, contact FDA at 1-888-FDA-VETS or online at www.fda.gov/reportanimalae.

ACTION

Ketamine Hydrochloride Injection is a rapid-acting agent whose pharmacological action is characterized by profound analgesia, normal pharyngeal-laryngeal reflexes, mild cardiac stimulation and respiratory depression. Skeletal muscle tone is variable and may be normal, enhanced or diminished. The anesthetic state produced does not fit into the conventional classification of stages of anesthesia, but instead Ketamine Hydrochloride Injection produces a state of unconsciousness which has been termed “dissociative” anesthesia in that it appears to selectively interrupt association pathways to the brain before producing somesthetic sensory blockade.

In contrast to other anesthetics, protective reflexes, such as coughing and swallowing are maintained under Ketamine Hydrochloride Injection anesthesia. The degree of muscle tone is dependent upon level of dose; therefore, variations in body temperature may occur. At low dosage levels there may be an increase in muscle tone and a concomitant slight increase in body temperature. However, at high dosage levels there is some diminution in muscle tone and a resultant decrease in body temperature, to the point where supplemental heat may be advisable.

In cats, there is usually some transient cardiovascular stimulation, increased cardiac output with slight increase in mean systolic pressure with little or no change in total peripheral resistance. At higher doses the respiratory rate is usually decreased.

The assurance of a patent airway is greatly enhanced by virtue of maintained pharyngeal-laryngeal reflexes. Although some salivation is occasionally noted, the persistence of the swallowing reflex aids in minimizing the hazards associated with ptyalism. Salivation may be effectively controlled with atropine sulfate in dosages of 0.04 mg/kg (0.02 mg/lb) in cats and 0.01 to 0.05 mg/kg (0.005 to 0.025 mg/lb) in subhuman primates.

Other reflexes, e.g., corneal, pedal, etc., are maintained during Ketamine Hydrochloride Injection anesthesia, and should not be used as criteria for judging depth of anesthesia. The eyes normally remain open with the pupils dilated. It is suggested that a bland ophthalmic ointment be applied to the cornea if anesthesia is to be prolonged.

Following administration of recommended doses, cats become ataxic in about 5 minutes with anesthesia usually lasting from 30 to 45 minutes at higher doses. At the lower doses, complete recovery usually occurs in 4 to 5 hours but with higher doses recovery time is more prolonged and may be as long as 24 hours.

In studies involving 14 species of subhuman primates represented by at least 10 anesthetic episodes for each species, the median time to restraint ranged from 1.5 [Aotus trivirgatus (night monkey) and Cebus capucinus (white-throated capuchin)] to 5.3 minutes [Macaca nemestrina (pig-tailed macaque)]. The median duration of restraint ranged between 20 and 55 minutes in all but five of the species studied. Total time from injection to end of restraint ranged from 43 [Saimiri sciureus (squirrel monkey)] to 183 minutes [Macaca nemestrina (pig-tailed macaque)] after injection. Recovery is generally smooth and uneventful. The duration is dose related.

By single intramuscular injection, Ketamine Hydrochloride Injection usually has a wide margin of safety in cats and subhuman primates. In cats, cases of prolonged recovery and death have been reported.

CLINICAL STUDIES

Ketamine hydrochloride injection has been clinically studied in subhuman primates in addition to those species listed under Dosage and Administration. Dosages for restraint in these additional species, based on limited clinical data, are: Cercopithecus aethiops (grivet), Papio papio (guinea baboon) 10 to 12 mg/kg; Erythrocebus patas patas (patas monkey) 3 to 5 mg/kg; Hylobates lar (white-handed gibbon) 5 to 10 mg/kg; Lemur catta (ringtailed lemur) 7.5 to 10 mg/kg; Macaca fuscata (Japanese macaque) 5 mg/kg; Macaca speciosa (stumptailed macaque) and Miopithecus talapoin (mangrove monkey) 5 to 7.5 mg/kg; and Symphalangus syndactylus (siamangs) 5 to 7 mg/kg.

STORAGE INFORMATION

Store at 20°C to 25°C (68°F to 77°F), with an excursion permitted between 15°C and 30°C (between 59°F and 86°F).

Protect from light. Do not use if precipitate appears. Use contents within 60 days of first puncture.

HOW SUPPLIED

Ketamine Hydrochloride Injection, 100 mg/mL is supplied in 10 mL vials.

Approved by FDA under ANADA # 200-029

Questions? (855) 724-3461

Distribued by:

Covetrus® North America

400 Metro Place North
Dublin, OH 43017
covetrus.com

© 2025 Covetrus, Inc. All rights reserved.
Made in India

CC-KetamineInjPI-01 REV: 0325

PACKAGE LABEL.PRINCIPAL DISPLAY PANEL

Covetrus

NDC: 11695-7039-1

Ketamine Hydrochloride Injection CIII

100 mg/mL

Caution: Federal law restricts this drug to use by or on the order of a licensed veterinarian.

Approved by FDA under ANADA # 200-029

Net Contents: 10 mL

Reorder #083479